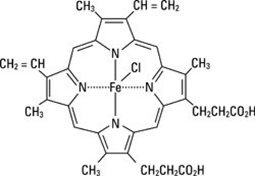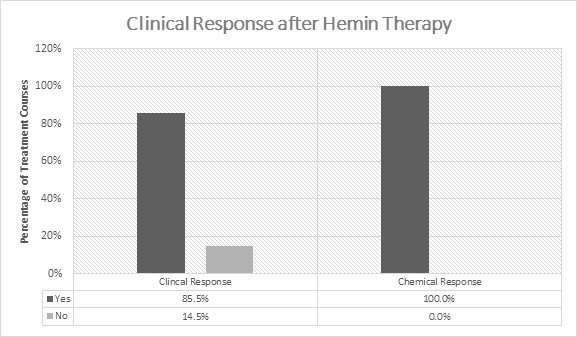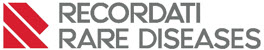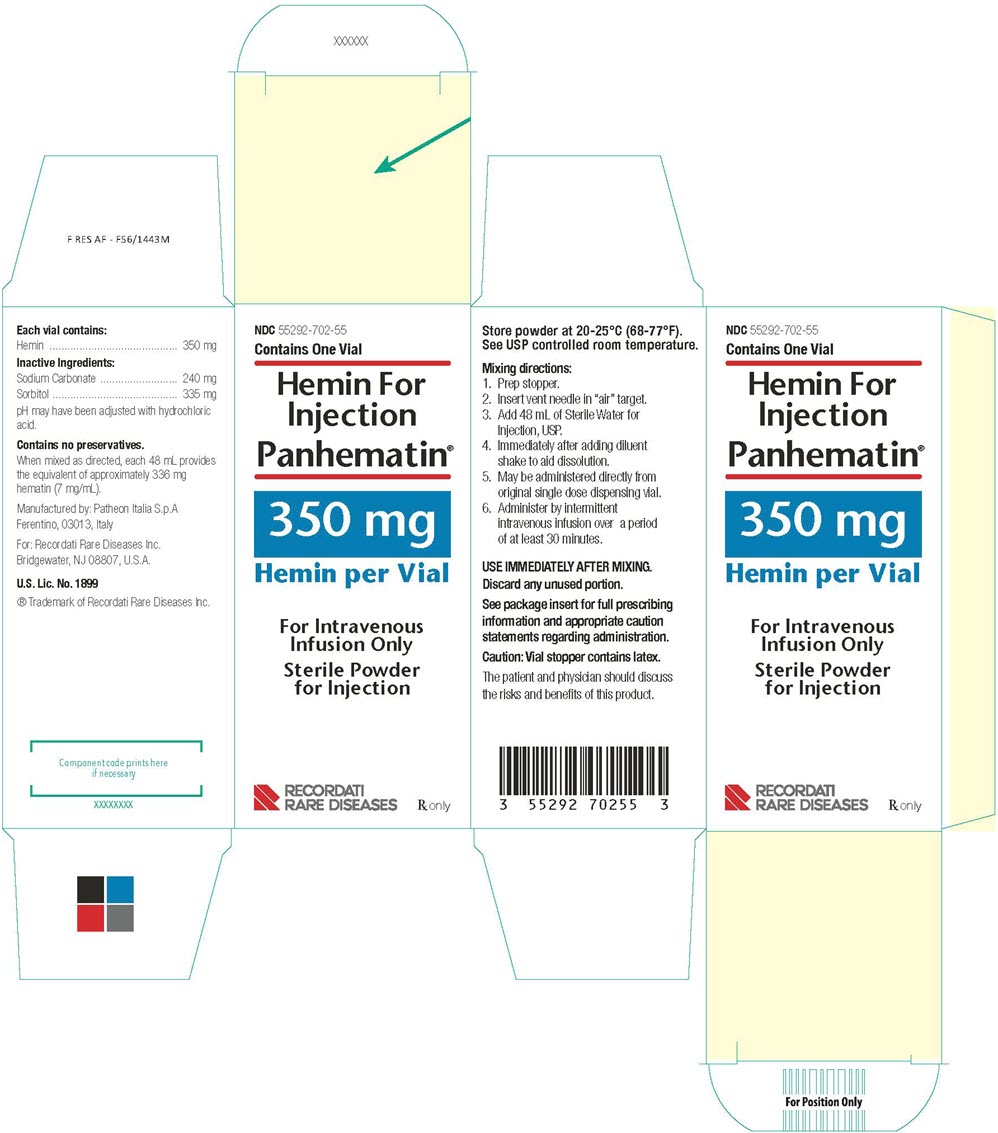 DRUG LABEL: Panhematin
NDC: 55292-702 | Form: POWDER, FOR SOLUTION
Manufacturer: Recordati Rare Diseases, Inc.
Category: prescription | Type: HUMAN PRESCRIPTION DRUG LABEL
Date: 20260226

ACTIVE INGREDIENTS: HEMIN 7 mg/1 mL
INACTIVE INGREDIENTS: SODIUM CARBONATE; SORBITOL; HYDROCHLORIC ACID

HIGHLIGHTS OF PRESCRIBING INFORMATION

These highlights do not include all the information needed to use PANHEMATIN safely and effectively. See full prescribing information for PANHEMATIN.
PANHEMATIN® (hemin for injection)
For intravenous infusion only.
Initial U.S. Approval: 1983

1 INDICATIONS AND USAGE

PANHEMATIN is a hemin for injection indicated for amelioration of recurrent attacks of acute intermittent porphyria temporally related to the menstrual cycle in susceptible women, after initial carbohydrate therapy is known or suspected to be inadequate. (1)

Limitations of Use

- Before administering PANHEMATIN, consider an appropriate period of carbohydrate loading (i.e., 400 g glucose/day for 1 to 2 days). (1)
- PANHEMATIN is not effective in repairing neuronal damage due to progression of porphyria attacks. (1)

2 DOSAGE AND ADMINISTRATION

For intravenous infusion only.

- Dose (2.1)
  - 1 to 4 mg/kg/day for 3 to 14 days based on the clinical signs. The standard dose in clinical practice is 3 to 4 mg/kg/day.
  - Repeat dose in more severe cases no earlier than every 12 hours. Do not exceed 6 mg/kg in any 24 hour period.
- Administration (2.2)
  - Use sterile 0.45 micron or smaller filter to remove any undissolved particulate matter.
  - The dose may be administered directly from the vial over a period of at least 30 minutes.
  - After the infusion, flush the vein with 100 mL of 0.9% NaCl.

3 DOSAGE FORMS AND STRENGTHS

PANHEMATIN is available as a sterile, lyophilized powder for reconstitution for injection. Each vial contains the equivalent of 350 mg hemin, 240 mg sodium carbonate and 335 mg of sorbitol.

When mixed as directed with Sterile Water for Injection, USP, each 48 mL provides the equivalent of approximately 336 mg hematin (7 mg/mL). (3)

4 CONTRAINDICATIONS

Do not use in patients with known hypersensitivity to PANHEMATIN. (4)

5 WARNINGS AND PRECAUTIONS

- Phlebitis is possible. Utilize a large arm vein or a central venous catheter for administration to minimize the risk of phlebitis. (5.1)
- Elevated iron and serum ferritin may occur. Monitor iron and serum ferritin in patients receiving multiple administrations of PANHEMATIN. (5.2)
- PANHEMATIN has transient and mild anticoagulant effect. Avoid concurrent anticoagulant therapy. (5.3)
- Reversible renal shutdown has been observed with an excessive hematin dose (12.2 mg/kg in a single infusion). Strictly follow recommended dosage guidelines. (5.4)
- PANHEMATIN may carry a risk of transmitting infectious agents, e.g., viruses, and theoretically, the Creutzfeldt-Jakob disease (CJD) agent. (5.5)

6 ADVERSE REACTIONS

Most common adverse reactions in >1% of patients are headache, pyrexia, infusion site reactions, and phlebitis. (6.1)

To report SUSPECTED ADVERSE REACTIONS, contact Recordati Rare Diseases Inc. at 1-888-575-8344 or FDA at 1-800-FDA-1088 or www.fda.gov/medwatch.

7 DRUG INTERACTIONS

Avoid CYP inducing drugs such as estrogens, barbituric acid derivatives and steroid metabolites which induce δ-aminolevulinic acid synthetase 1 (ALAS1) through a feedback mechanism. (7)

FULL PRESCRIBING INFORMATION

1 INDICATIONS AND USAGE

PANHEMATIN is a hemin for injection indicated for the amelioration of recurrent attacks of acute intermittent porphyria temporally related to the menstrual cycle in susceptible women, after initial carbohydrate therapy is known or suspected to be inadequate.

Limitations of Use

- Before administering PANHEMATIN, consider an appropriate period of carbohydrate loading (i.e., 400 g glucose/day for 1 to 2 days) [See Dosage and Administration (2.1)].
- Attacks of porphyria may progress to a point where irreversible neuronal damage has occurred. PANHEMATIN therapy is intended to prevent an attack from reaching the critical stage of neuronal degeneration. PANHEMATIN is not effective in repairing neuronal damage.

2 DOSAGE AND ADMINISTRATION

For intravenous infusion only.

2.1 Dosing

- PANHEMATIN should only be used by or in consultation with physicians experienced in the management of porphyrias.
- Before PANHEMATIN therapy is begun, the presence of acute porphyria must be diagnosed using the following criteria:
1. Presence of clinical symptoms suggestive of acute porphyric attack.
2. Quantitative measurement of porphobilinogen (PBG) in urine. The single-void urine sample should be refrigerated or frozen without additives and shielded from light for subsequent quantitative δ-aminolevulinic acid (ALA), PBG, and total porphyrin determinations. (Note: the classical Watson-Schwartz or Hoesch tests are considered to be less reliable).
- Clinical benefit from PANHEMATIN depends on prompt administration. For mild porphyric attacks (mild pain, no vomiting, no paralysis, no hyponatremia, no seizures), a trial of glucose therapy is recommended while awaiting hemin treatment or if hemin is unavailable. For moderate to severe attacks, immediate hemin treatment is recommended. Symptoms of severe attacks are severe or prolonged pain, persistent vomiting, hyponatremia, convulsion, psychosis, and neuropathy. In addition to treatment with PANHEMATIN, consider other necessary measures such as the elimination of triggering factors.
- The dose of PANHEMATIN is 1 to 4 mg/kg/day of hematin for 3 to 14 days based on the clinical signs. The standard dose in clinical practice is 3 to 4 mg/kg/day. In more severe cases this dose may be repeated no earlier than every 12 hours. Do not exceed 6 mg/kg of hematin in any 24 hour period. After reconstitution each mL of PANHEMATIN contains the equivalent of approximately 7 mg of hematin (see dosage calculation table below).

Dosage Calculation Table

1 mg hematin equivalent = 0.14 mL PANHEMATIN

2 mg hematin equivalent = 0.28 mL PANHEMATIN

3 mg hematin equivalent = 0.42 mL PANHEMATIN

4 mg hematin equivalent = 0.56 mL PANHEMATIN

- Monitor urinary concentrations of the following compounds during PANHEMATIN therapy. Effectiveness is demonstrated by a decrease in one or more of the following compounds.
  ALA - δ-aminolevulinic acid
  PBG - porphobilinogen
  Uroporphyrin
  Coproporphyrin

2.2 Preparation and Administration

- Because PANHEMATIN contains no preservative and undergoes rapid chemical decomposition in solution, it must be reconstituted immediately before use.
- Reconstitute PANHEMATIN by aseptically adding 48 mL of Sterile Water for Injection, USP, to the dispensing vial. Shake the vial well for a period of 2 to 3 minutes to aid dissolution.
- PANHEMATIN may be administered directly from the vial. After the first withdrawal from the vial, discard any solution remaining.
- Parenteral drug products should be inspected visually for particulate matter and discoloration prior to administration, whenever solution and container permit. Since reconstituted PANHEMATIN is not transparent, any undissolved particulate matter is difficult to see when inspected visually. Therefore, terminal filtration through a sterile 0.45 micron or smaller filter is recommended.
- Do not add other drug or chemical agent to a PANHEMATIN fluid admixture.
- Infuse the dose over a period of at least 30 minutes via a separate line.
- After the infusion, flush the vein with 100 mL of 0.9% NaCl.

3 DOSAGE FORMS AND STRENGTHS

PANHEMATIN is available as a sterile, lyophilized black powder in single dose dispensing vials. Each vial contains the equivalent of 350 mg hemin, 240 mg sodium carbonate and 335 mg of sorbitol. When mixed as directed with Sterile Water for Injection, USP, each 48 mL provides the equivalent of approximately 336 mg hematin (7 mg/mL).

4 CONTRAINDICATIONS

PANHEMATIN is contraindicated in patients with known hypersensitivity to this drug.

5 WARNINGS AND PRECAUTIONS

5.1 Risk of Phlebitis

A large arm vein or a central venous catheter should be utilized for the administration of PANHEMATIN to minimize the risk of phlebitis.

Since reconstituted PANHEMATIN is not transparent, any undissolved particulate matter is difficult to see when inspected visually. Therefore, terminal filtration through a sterile 0.45 micron or smaller filter is recommended. [See Dosage and Administration (2.2)]

5.2 Iron and Serum Ferritin

Because increased levels of iron and serum ferritin have been reported in post-marketing experience, physicians must monitor iron and serum ferritin in patients receiving multiple administrations of PANHEMATIN [See Adverse Reactions (6.2)]. In case of elevated iron or serum ferritin levels, consider iron chelation therapy.

5.3 Anticoagulant Effects

Because PANHEMATIN has exhibited transient, mild anticoagulant effects during clinical studies, avoid concurrent anticoagulant therapy. The extent and duration of the hypocoagulable state induced by PANHEMATIN has not been established.

5.4 Renal Effects

Recommended dosage guidelines should be strictly followed. Reversible renal shutdown has been observed in a case where an excessive hematin dose (12.2 mg/kg) was administered in a single infusion. Oliguria and increased nitrogen retention occurred although the patient remained asymptomatic. No worsening of renal function has been seen with administration of recommended dosages of hematin.

5.5 Transmissible Infectious Agents

Because PANHEMATIN is made from human blood, it may carry a risk of transmitting infectious agents, e.g., viruses, the variant Creutzfeldt-Jacob disease (vCJD) agent, and theoretically the Creutzfeldt-Jacob disease (CJD) agent. The risk that this product may transmit an infectious agent has been reduced by screening blood donors for prior exposure to certain viruses, by testing for the presence of certain current virus infections, and by inactivating certain viruses. Despite these measures, this product can still potentially transmit disease. There is also the possibility that unknown infectious agents may be present in the product.

All infections thought by a physician possibly to have been transmitted by this product should be reported by the physician or other healthcare provider to Recordati Rare Diseases at 1-888-575-8344.

6 ADVERSE REACTIONS

The most common adverse reactions (occurring in >1% of patients) are: headache, pyrexia, infusion site reactions, and phlebitis.

6.1 Clinical Trials Experience

Because clinical trials are conducted under widely varying conditions, adverse reaction rates observed in the clinical trials of a drug cannot be directly compared to rates in the clinical trials of another drug and may not reflect the rates observed in practice.

The safety of PANHEMATIN use was evaluated in a compassionate use study. A total of 130 patients were treated with hemin for acute attacks, prophylaxis or both. Of those, 111 patients were administered hemin for treatment of 305 acute porphyria attacks and to 40 patients for prophylaxis. The majority (92%) of patients were Caucasian. Most (72%) were female; all adult patients had a mean age ± SD of 40.3 ± 12.3 years. Proportionally more females (15 out of 19) received prophylaxis or a combination of acute treatment and prophylaxis (19 out of 21). For the treatment of acute attacks, patients received 2 to 4 mg/kg/day PANHEMATIN intravenously for 1 to 9 doses. For prophylaxis patients, the most common doses were weekly or biweekly infusions.

Table 1 summarizes adverse reactions occurring in >1% of patients treated with PANHEMATIN, categorized by body system and order of decreasing frequency.

Table 1: Adverse Reactions in >1% of Patients Treated with PANHEMATIN
System Organ Class Preferred Term | Adverse Events N (% of Total Adverse Events)
Description | Total | Possibly or Probably Related to Treatment
Infections and infestations
Cellulitis | 3 (1.5%) | 2 (1.0%)
Nervous System Disorders
Headache | 18 (9.2%) | 5 (2.6%)
Vascular Disorders
Phlebitis / Injection site phlebitis | 7 (3.6%) | 6 (3.1%)
Skin and subcutaneous tissue disorders
Rash | 3 (1.5%) | 3 (1.5%)
General Disorders and Administration Site Conditions
Pyrexia | 9 (4.6%) | 6 (3.1%)
Catheter-related Complication | 7 (3.6%) | 3 (1.5%)

6.2 Postmarketing Experience

The following adverse reactions associated with the use of PANHEMATIN were identified in open-label clinical trials or postmarketing reports. Because these reactions were reported voluntarily from a population of uncertain size, it is not always possible to estimate their frequency reliably or to establish a causal relationship to drug exposure.

Blood and Lymphatic System Disorders: thrombocytopenia, coagulopathy (including prolonged prothrombin time and prolonged partial thromboplastin time), and hemolysis

Immune System Disorders: hypersensitivity reactions including a report of infusion-related anaphylactoid reaction presenting as circulatory collapse

Vascular Disorders: injection site venous thrombosis including some that occurred in large veins such as venae cavae

General Disorders and Administration Site Conditions: infusion site reactions (such as erythema, pain, bleeding and extravasation)

Metabolism and Nutrition Disorders: iron overload and serum ferritin increased [See Warnings and Precautions (5.2)]

7 DRUG INTERACTIONS

PANHEMATIN therapy is intended to limit the rate of porphyria/heme biosynthesis possibly by inhibiting the enzyme δ-aminolevulinic acid synthetase 1 (ALAS1) [See Clinical Pharmacology (12.1)]. Most of the heme synthesized in liver is used for the production of cytochrome P450 (CYP) enzymes. Therefore, avoid CYP inducing drugs (such as estrogens, barbituric acid derivatives and steroid metabolites) while on PANHEMATIN therapy, because these drugs increase the activity of ALAS leading to induction of ALAS1 through a feedback mechanism.

8 USE IN SPECIFIC POPULATIONS

8.1 Pregnancy

Risk Summary

About 50% of the women with acute intermittent porphyria experience an acute attack of porphyria in pregnancy and/or the puerperium. It is most severe in early pregnancy and the puerperium, and can result in fatal outcome. Although anecdotal evidence suggests safe use of hematin during pregnancy, the available human data is not sufficient to establish the presence or absence of drug-associated risk. Animal reproduction studies have not been conducted with hematin. It is also not known whether hematin can cause fetal harm when administered to a pregnant woman or can affect reproduction capacity. PANHEMATIN should be given to a pregnant woman only if clearly needed.

Avoid administering hematin in severe pre-eclampsia because of a theoretical risk of potentiation of the coagulation disorder [see Warnings and Precautions (5.3)].

In the U.S. general population, the estimated background risk of major birth defects and miscarriage in clinically recognized pregnancies is 2-4% and 15-20%, respectively.

8.2 Lactation

Risk Summary

It is not known whether this drug is excreted in human milk. Because many drugs are excreted in human milk, the developmental and health benefits of breastfeeding should be considered along with the mother's clinical need for PANHEMATIN and any potential adverse effects on the breastfed child from PANHEMATIN or from the underlying maternal condition.

8.4 Pediatric Use

Safety and effectiveness in pediatric patients under 16 years of age have not been established.

8.5 Geriatric Use

Clinical data for subjects aged 65 and over was not sufficient to determine whether they respond differently from younger subjects. Other reported clinical experience has not identified differences in response between the elderly and younger patients. In general, dose selection for an elderly patient should be cautious, usually starting at the low end of the dosing range, reflecting the greater frequency of decreased hepatic, renal, or cardiac function, and of concomitant disease or other drug therapy.

10 OVERDOSAGE

Reversible renal shutdown has been observed in a case where an excessive hematin dose (12.2 mg/kg) was administered in a single infusion [see Warnings and Precautions (5.4)]. Treatment of this case consisted of ethacrynic acid and mannitol.

11 DESCRIPTION

PANHEMATIN (hemin for injection) is an enzyme inhibitor derived from processed red blood cells. Hemin for injection was known previously as hematin. The term hematin has been used to describe the chemical reaction product of hemin and sodium carbonate solution. Hemin and hematin are iron containing metalloporphyrin complexes with either bound chloride or hydroxide ions, respectively. Chemically hemin is represented as chloro [7,12-diethenyl-3,8,13,17-tetramethyl- 21H,23H-porphine-2,18-dipropanoato(2-)-N^21,N^22,N^23,N^24] iron. The structural formula for hemin is:

PANHEMATIN is formatted as a sterile, lyophilized powder for intravenous administration after reconstitution. Each dispensing vial of PANHEMATIN contains the equivalent of 350 mg hemin, 240 mg sodium carbonate and 335 mg of sorbitol. The pH may have been adjusted with hydrochloric acid. When mixed as directed with Sterile Water for Injection, USP, each 48 mL provides the equivalent of approximately 336 mg hematin (7 mg/ mL). The product contains no preservatives.

12 CLINICAL PHARMACOLOGY

12.1 Mechanism of Action

Heme acts to limit the hepatic and/or marrow synthesis of porphyrin. This action is likely due to the inhibition of δ-aminolevulinic acid synthetase, the enzyme which limits the rate of the porphyrin/heme biosynthetic pathway. The exact mechanism by which hematin produces symptomatic improvement in patients with acute episodes of the hepatic porphyrias has not been elucidated.

PANHEMATIN therapy for the acute porphyrias is not curative. After discontinuation of PANHEMATIN treatment, symptoms generally return although in some cases remission is prolonged. Some neurological symptoms have improved weeks to months after therapy although little or no response was noted at the time of treatment.

12.3 Pharmacokinetics

Following intravenous administration of hematin in non-jaundiced human patients, an increase in fecal urobilinogen can be observed which is roughly proportional to the amount of hematin administered. This suggests an enterohepatic pathway as at least one route of elimination. Bilirubin metabolites are also excreted in the urine following hematin injections.

Other aspects of human pharmacokinetics have not been defined.

13 NONCLINICAL TOXICOLOGY

13.1 Carcinogenesis, Mutagenesis, Impairment of Fertility

PANHEMATIN was not mutagenic in bacteria systems in vitro and was not clastogenic in mammalian systems in vitro and in vivo. No data are available on potential for carcinogenicity or impairment of fertility in animals.

14 CLINICAL STUDIES

The effectiveness of PANHEMATIN for the amelioration of recurrent attacks of acute intermittent porphyria was evaluated in five open-label studies, one compassionate-use study, case reports, and an observational study investigating patient reported outcomes in patients with acute porphyrias.

Open-Label Studies

In the initial 5 open-label studies,^1-5 99 patients with acute porphyrias (72 with AIP) were treated with 3-4 mg/kg/day of hemin once or twice daily. Of the 99 patients in these studies, 30 received prior or concomitant glucose administration. Patients experienced a clinical response in 85.5% (141/165) of treatment courses (Figure 1). Clinical response was defined by improvement of symptoms and reduction in pain. All patients experienced a chemical response which was defined as normalization of urinary aminolevulinic acid (ALA) and porphobilinogen (PBG).

Watson et al.^1 studied the use of hemin treatment in 15 patients with acute porphyrias, of whom 11 were with AIP. Seven patients were female and four were male with an age range of 19-45 years with biochemical evidence of AIP. Preparations of 4 mg/kg IV of hemin were infused at 12- or 24-hour intervals for 1 to 4 days after trials of glucose of various durations and dosages in all patients. All patients, with exception of one, experienced a clear clinical response most of which was rapid after hemin infusion. All patients also demonstrated a chemical response based on 58%-100% reduction in urinary ALA and PBG levels.

Pierach et al.^2 examined the use of 2 to 4 mg/kg of hemin IV in 57 patients with acute porphyrias, of whom 43 were with AIP. Out of 82 individual acute intermittent porphyria attacks with 476 hemin infusions (82 treatment courses) administered, a clinical response was seen in 74 (90%) acute attacks. A chemical response was seen for those patients who had elevated urinary ALA and PBG levels prior to hemin treatment.

McColl et al.^3 reported the use of 4 mg/kg of hemin IV given either every 12 or 24 hours for three to five days in the treatment of 13 attacks of acute porphyria in eight patients. Seven of these 8 patients had AIP. Five patients with AIP were female and two were male with a mean age of 25 years (range 19-31 years). All patients had biochemical and clinical evidence of an attack of acute porphyria at the time of hemin administration. All patients had a chemical response of approximately 50% reduction in urinary ALA and PBG from pre-treatment values. In addition, clinical response was seen after hemin treatment in a total of 7 attacks in 5 AIP patients.

Lamon et al.^4 reported on 12 patients with acute porphyrias, of whom 11 were with AIP. These AIP patients received 190 infusions of approximately 2 to 4 mg/kg of hemin IV given every 12 or 24 hours for 3 to 13 days as 20 separate courses of treatment, when high carbohydrate intake (300 g for a minimum of 72 hours) and supportive measures were unsuccessful. Urinary ALA and PBG levels were collected as well as clinical signs and symptoms of AIP recorded. Out of 20 treatment courses for acute attacks, there was a clinical response in 14. All patients had significant reductions in ALA and/or PBG levels after hemin treatment (p-value in the range from less than 0.001 to 0.05).

In another study by Lamon et al.^5 seven patients with acute attacks of porphyria were administered 11 hemin courses (each course: 1 mg/kg every 24 hours for 3 to 13 days). Before and during hemin administration, patients were maintained on a 250-300 g/24H carbohydrate diet. Patients had elevated urinary ALA and PBG treatment and clinical evidence of an acute attack. Chemical response of a decrease in ALA and PBG occurred in every patient (except one PBG value in one patient) when treatment lasted 5 days or longer (p<0.001).

Figure 1: Efficacy Data on Hemin in Acute Intermittent
Porphyria from 5 Open-Label Studies

Compassionate Use Study

In the compassionate use, multi-center, open-label, non-comparative study^6, 130 patients were enrolled with a diagnosis of acute porphyria and were treated with hemin. The patients were administered hemin for acute attacks [N=90 (69%)], prophylaxis [N=19 (15%)], or both [N=21 (16%)]. There was a subset of patients in the "both" group (acute attacks and prophylaxis) who were treated for acute attacks prior to receiving prophylactic treatment. Seventy-two percent of the patients were female and 28% were male. Hemin was administered to 111 patients (enrolled in the "acute attack" and the "both" treatment groups) for the treatment of 305 acute attacks and to 40 patients (enrolled in the "prophylaxis" and the "both" treatment groups) for prophylactic treatment. Out of the 40 patients who received prophylaxis, 19 received prophylaxis only and 21 patients were treated for up to 3 acute attacks prior to receiving prophylactic treatment. Prophylaxis treatment varied greatly in frequency with the most common hemin regimen given once a week. Clinical response was achieved if the physician determined that the admitting symptoms were resolved, there was a clinically acceptable response, or the patient went into remission.

A physician-assessed clinical response was achieved for all acute attacks in 81 (73%) of 111 patients. Ninety-four patients (85%) of 111 had ≥1 clinical response and 17 patients (15%) of 111 had no response. Among 31 of 40 patients who received hemin prophylaxis for >1 month, 21 (68%) did not require subsequent hemin treatment for acute attacks.

Case Reports

In 234 courses, patients received hemin therapy as normally prescribed by their physicians with the majority dosed between the recommended range of 3 mg/kg/day to 4 mg/kg/day for at least one course of treatment. In these patients, hemin treatment was administered immediately in 33% of recipients, within 1 day of symptom onset in 50%, and within 3 days in 75%. These groups were not mutually exclusive. Most patients [108/111 (97.3%)] received a dose of at least 3 mg/kg/day and only 3 patients (2.7%) received a dose of hemin less than 2 mg/kg/day. There were 6 patients (5.4%) who were administered doses exceeding 6 mg/kg/day for 1 or more treatment courses.

Observational Patient Reported Outcomes Study

An observational study investigated patient reported outcomes in 108 patients with acute porphyrias.^7 Out of 108 patients, 90 patients were with AIP and reported the following:

- 55% percent reported having received hemin during acute attacks, and 74% of these patients assessed PANHEMATIN therapy as very successful in the treatment of abdominal pain and other symptoms.
- 50% reported having received treatment with opiates during an acute attack, and 44% of these patients reported that opiates were effective.

Hemin therapy effectiveness was assessed along with glucose infusions, high carbohydrate diets, and pain medications on a scale from zero being least effective to 10 highly effective. Hemin infusions received a 7.9, glucose infusions a 4.4 (p=0.0781), high carbohydrate diets a 4.7 (p=0.0021), and pain medications a 4.2 (p=0.0049).

15 REFERENCES

1. Watson, CJ, et al., Use of Hematin in the Acute Attack of the "Inducible" Hepatic Porphyrias, Adv Intern Med. 1978;23:265-286.
2. Pierach CA, Bossenmaier I, Cardinal R, Weimer M, Watson CJ. Hematin therapy in porphyric attacks. Klinische Wochenschrift. 1980;58(16):829-832.
3. McColl KE, Moore MR, Thompson GG, Goldberg A. Treatment with haematin in acute hepatic porphyria. The Quarterly journal of medicine. 1981;50(198):161-174.
4. Lamon, JM, Hematin Therapy for Acute Porphyria, Medicine. 1979;58(3):252-269.
5. Lamon JM. Hematin Therapy in Acute Porphyria. Clin Res. 1977;25(3):471A.
6. Anderson, KE and Collins, S, Open-Label Study of Hemin for Acute Porphyria: Clinical Practice Implications. American Journal of Medicine. 2006;119(9):801.
7. Bonkovsky HL, Maddukuri VC, Yazici C, Anderson KE, Bissell M, et al. Acute porphyrias in the USA: features of 108 subjects from porphyrias consortium. Am J Med. 2014;127(12):1233-1241.

16 HOW SUPPLIED/STORAGE AND HANDLING

PANHEMATIN is supplied as a sterile, lyophilized black powder in single dose dispensing vials (NDC 55292-702-54) in a carton (NDC 55292-702-55).

The vial stopper contains natural rubber latex.

Store lyophilized powder at 20-25°C (68-77°F).

17 PATIENT COUNSELING INFORMATION

- Advise the patient not to take drugs such as estrogens (e.g., oral contraceptives), barbiturates (drugs which help them to sleep and drugs sometimes used to treat epilepsy) or steroids (body hormone-like drugs), because this can trigger an attack or make the attack worse.
- Advise a female patient to inform the prescriber if she is pregnant or planning to become pregnant.

Manufactured by:
Patheon Italia S.p.A
Ferentino, 03013, Italy

For:
Recordati Rare Diseases Inc.
Bridgewater, NJ 08807, U.S.A.

U.S. Lic. No. 1899

Panhematin® is a registered trademark of Recordati Rare Diseases Inc.

PRINCIPAL DISPLAY PANEL - 350 mg Vial Carton

NDC 55292-702-55

Contains One Vial

Hemin For
Injection

Panhematin®

350 mg
Hemin per Vial

For Intravenous
Infusion Only

Sterile Powder
for Injection

RECORDATI
RARE DISEASES

Rx only